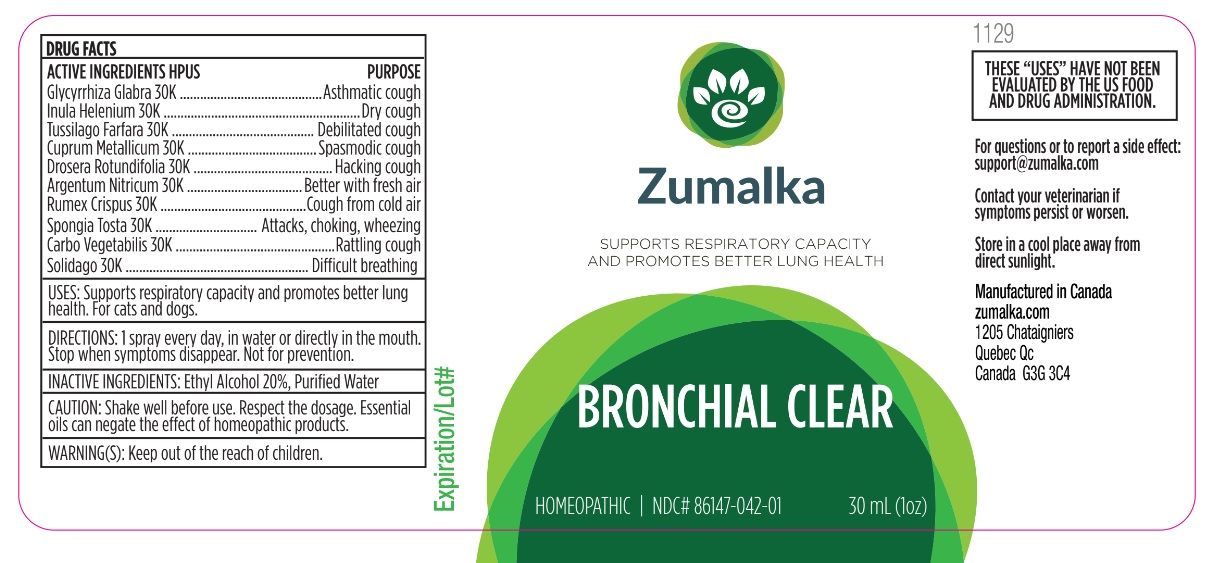 DRUG LABEL: Bronchial Clear
NDC: 86147-042 | Form: LIQUID
Manufacturer: Groupe Cyrenne Inc.
Category: homeopathic | Type: OTC ANIMAL DRUG LABEL
Date: 20251120

ACTIVE INGREDIENTS: GLYCYRRHIZA GLABRA 30 [kp_C]/30 mL; INULA HELENIUM ROOT 30 [kp_C]/30 mL; TUSSILAGO FARFARA 30 [kp_C]/30 mL; COPPER 30 [kp_C]/30 mL; DROSERA ROTUNDIFOLIA WHOLE 30 [kp_C]/30 mL; ACTIVATED CHARCOAL 30 [kp_C]/30 mL; RUMEX CRISPUS ROOT 30 [kp_C]/30 mL; SPONGIA OFFICINALIS SKELETON, ROASTED 30 [kp_C]/30 mL; SOLIDAGO VIRGAUREA FLOWERING TOP 30 [kp_C]/30 mL; SILVER NITRATE 30 [kp_C]/30 mL
INACTIVE INGREDIENTS: ALCOHOL; WATER

Active ingredients Purpose

Glycyrrhiza Glabra 30k Asthmatic cough

Inula Helenium 30k Dry cough

Tussilago Farfara 30k Debilitated cough

Cuprum Metallicum 30k Spasmodic cough

Drosera Rotundifolia 30k Hacking cough

Argentum Nitricum 30k Better with fresh air

Rumex Crispus 30k Cough from cold air

Spongia Tosta 30k Attacks, choking, wheezing

Carbo Vegetabilis 30k Rattling cough

Solidago 30k Difficult breathing

Uses

Supports respiratory capacity and promotes better lung health. For cats and dogs only.

Warnings

Keep out of reach of children.

Direction

1 spray every day, in water or directly in the mouth. Stop when symptoms disappear. Not for prevention.

Inactive ingredients

Ethyl alcohol 20%, purified water

Cautions

Shake well before use. Respect the dosage. Essential oils can negate the effects of homeopathic products. Store in a cool place away from direct sunlight.